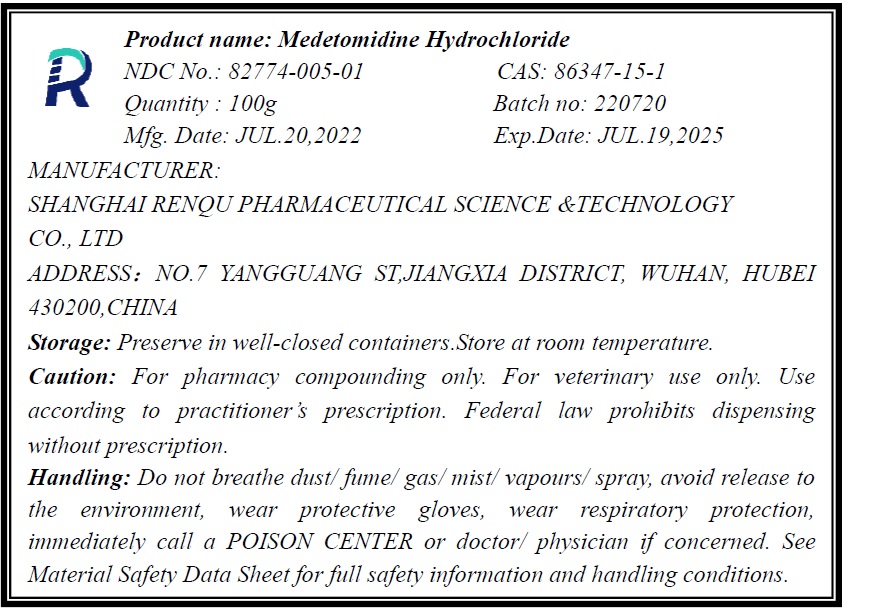 DRUG LABEL: Medetomidine Hydrochloride
NDC: 82774-005 | Form: POWDER
Manufacturer: Shanghai Renqu Pharmaceutical Science & Technology Co., Ltd.
Category: other | Type: BULK INGREDIENT - ANIMAL DRUG
Date: 20220908

ACTIVE INGREDIENTS: MEDETOMIDINE HYDROCHLORIDE 1 g/1 g

Medetomidine Hydrochloride